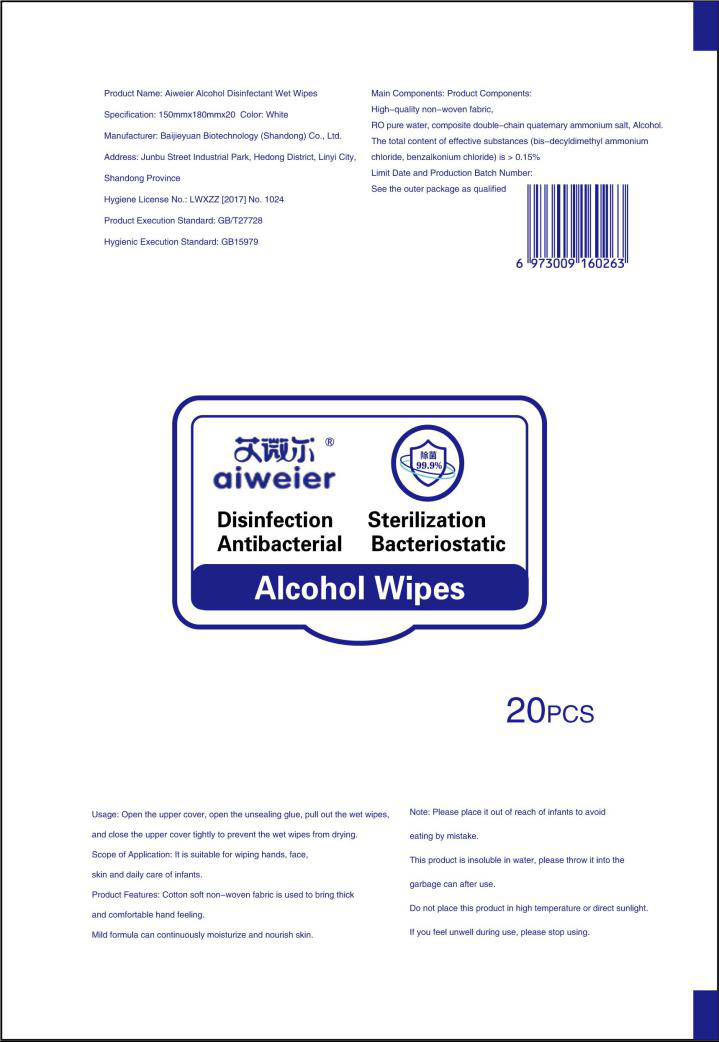 DRUG LABEL: Aiweier Alcohol Wipes
NDC: 55490-004 | Form: CLOTH
Manufacturer: Baijieyuan Biotechnology (Shandong) Co., Ltd.
Category: otc | Type: HUMAN OTC DRUG LABEL
Date: 20200610

ACTIVE INGREDIENTS: BRONOPOL 0.0969 g/20 1; BENZALKONIUM CHLORIDE 0.0969 g/20 1; ALCOHOL 242.25 g/20 1; BENZETHONIUM CHLORIDE 0.0646 g/20 1; PHENOXYETHANOL 0.1938 g/20 1
INACTIVE INGREDIENTS: BUTYLENE GLYCOL; ALOE; WATER; GLYCERIN

DOSAGE AND ADMINISTRATION

Store below 110°F (43°C)

INACTIVE INGREDIENT

Butane-1,3-diol

Glycerol

Aloe extract

Pure water

INDICATIONS AND USAGE

Open the upper cover, cpen the unsealing glue, pull out the wet wipes,and dose the upper cover tightly to prevent the wet wipes from drying.

ACTIVE INGREDIENT

Bronopol

Benzethonium chloride

2-Phenoxyethanol

Quaternary ammonium compounds,benzyl-C12-16-alkyldimethyl,chlorides

Ethyl alcohol

keep out of reach of children

PURPOSE

Disinfection
Sterilization
No Rinseing

WARNINGS

For external use only,Keep away from heat or flame.